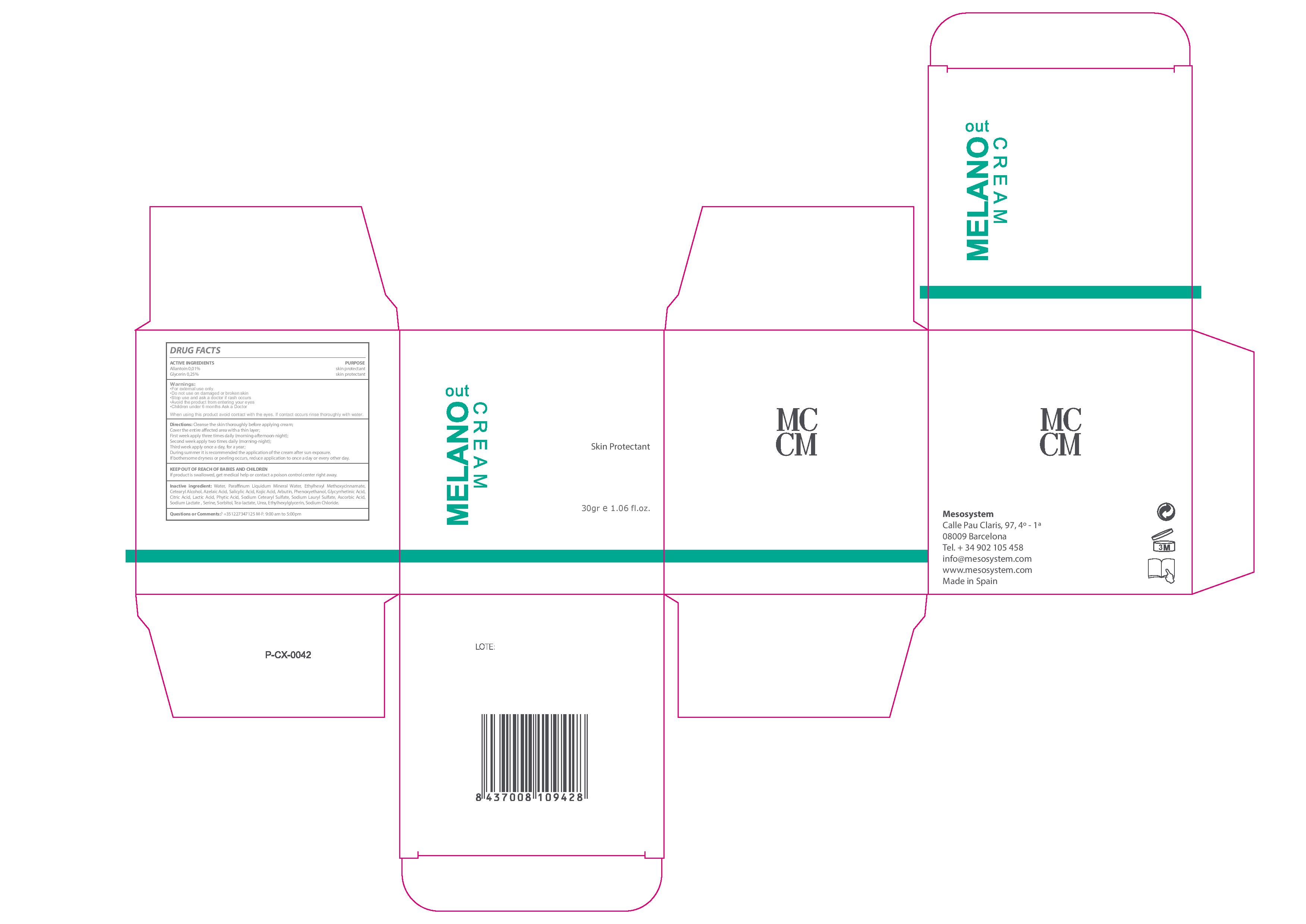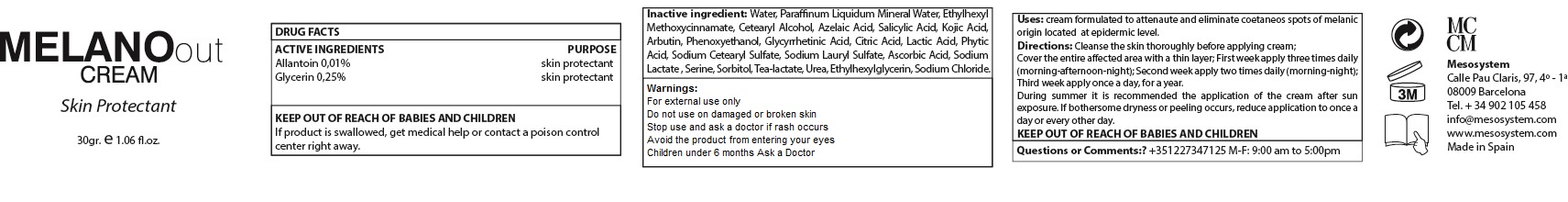 DRUG LABEL: Melano Out Cream
NDC: 70663-007 | Form: CREAM
Manufacturer: MESO SYSTEM S.A.
Category: otc | Type: HUMAN OTC DRUG LABEL
Date: 20161217

ACTIVE INGREDIENTS: ALLANTOIN 0.1 mg/1 mL; GLYCERIN 0.25 mg/1 mL
INACTIVE INGREDIENTS: SALICYLIC ACID 1 mg/1 mL; ETHYLHEXYL METHOXYCRYLENE 6 mg/1 mL; WATER 52.19 mg/1 mL; AZELAIC ACID 15 mg/1 mL; PHENOXYETHANOL 0.9 mg/1 mL; ETHYLHEXYLGLYCERIN 0.1 mg/1 mL; MINERAL OIL 13 mg/1 mL; CETYL ALCOHOL 5.4 mg/1 mL; KOJIC ACID 1 mg/1 mL; CITRIC ACID MONOHYDRATE 0.5 mg/1 mL; LACTIC ACID 0.5 mg/1 mL; SODIUM LACTATE 0.25 mg/1 mL; SORBITOL, L- 0.25 mg/1 mL; TRIETHANOLAMINE LACTATE 0.25 mg/1 mL; ARBUTIN 0.9 mg/1 mL; ALLANTOIN GLYCYRRHETINIC ACID 0.6 mg/1 mL; FYTIC ACID 0.5 mg/1 mL; SODIUM CETOSTEARYL SULFATE 0.3 mg/1 mL; SODIUM LAURYL SULFATE 0.3 mg/1 mL; ASCORBIC ACID 0.25 mg/1 mL; SERINE 0.25 mg/1 mL; HYDROXYETHYL UREA 0.25 mg/1 mL; SODIUM CHLORIDE 0.05 mg/1 mL

Melano Out Cream

Warnings

Stop use and ask a Doctor if rash occurs

WARNINGS

- For external use only.
- Do no use on damaged or broken skin
- Stop use and ask a doctor if rash occurs
- Avoid the product from entering your eyes
- Children under 6 months Ask a Doctor

USES

- Cream formulated to atenuate and eliminate the coetaneus spot of melanic origin located at the epidermic level

- Keep out of the reach of chuldren.
- In case of overdose get medical help or Contact a Poison Control Center right away.

DIRECTIONS

- Clean the skin thoroughly before applying the cream.
- Cover the entire affected area with a thin layer. First week apply three times daily (morning-afternoon-night). Second week apply two times daily (morning-night). Third week apply once a day for one year.
- During summer it is recommended the application of the cream after sun exposure. If bothersome dryness or peeling occurs, reduce application to once a day or every other day

QUESTIONS OR COMMENTS ?

- +35 1227347125 M-F: 9:00 am to 5:00 pm

ACTIVE INGREDIENTS

Active Ingredients Purpose

Allantoin 0.01%................................Skin Protectant

Glycerin 0.25%.................................Skin Protectant

Inactive Ingredients

Water, Azelaic Acid, Mineral Oil, Ethylhexyl Methoxycinnamate, Cetearyl Alcohol, Salicylic Acid, Kojic Acid,,Arbutin, Phenoxyethanol, Glycyrrhetinic Acid, Citric Acid, Lactic Acid, Phytic Acid, Sodium Cetearyl Sulfate, Sodium Lauryl Sulfate, Ascorbic Acid, Sodium, Lactate, Serine, Sorbitol, Tea-lactate, Urea, Ethylhexylglycerin, Sodium Chloride

INDICATIONS AND USAGE

- Cream formulated to atenuate and eliminate the coetaneus spot of melanic origin located at the epidermic level

Melano Out Cream

Skin Protecting